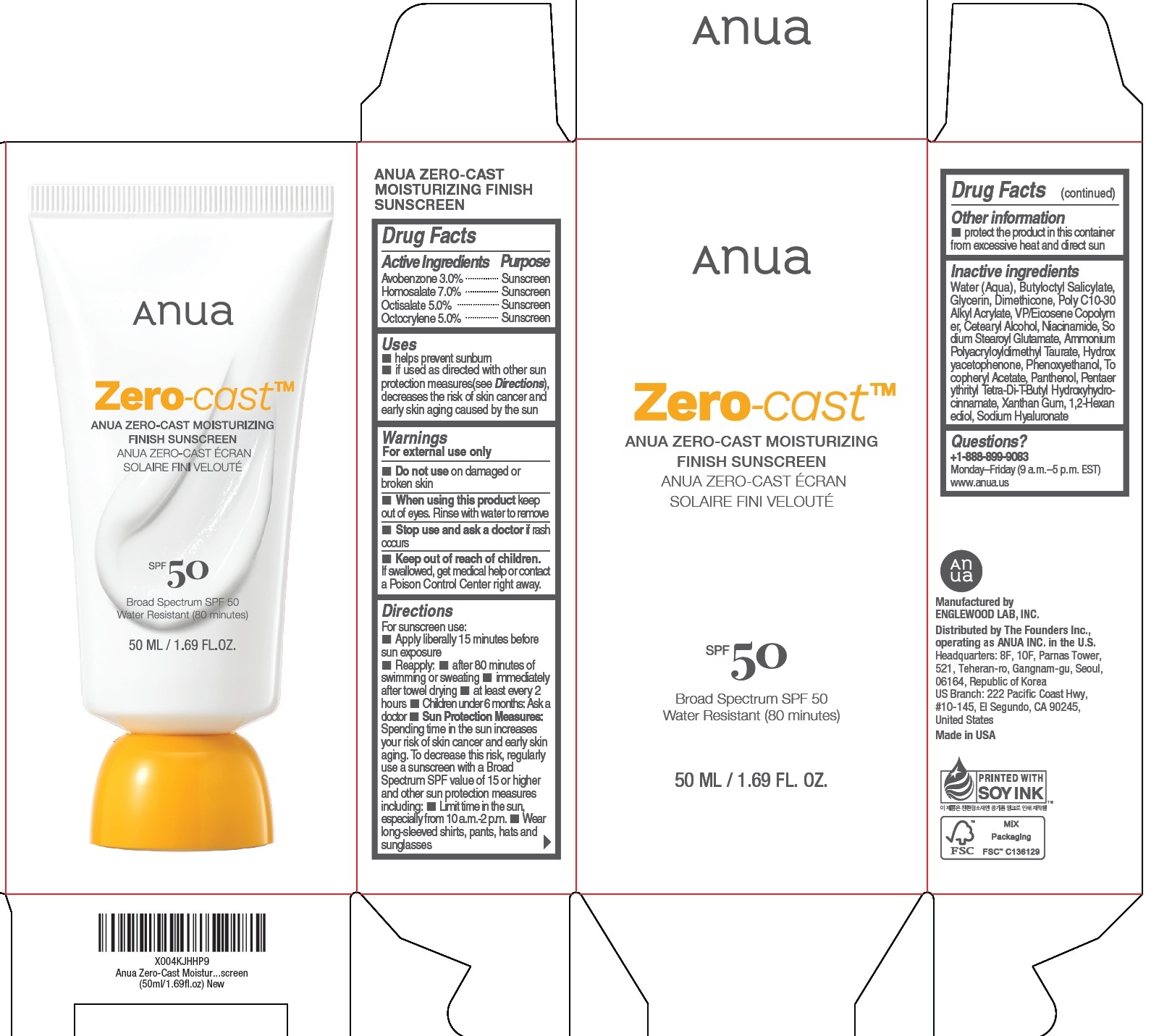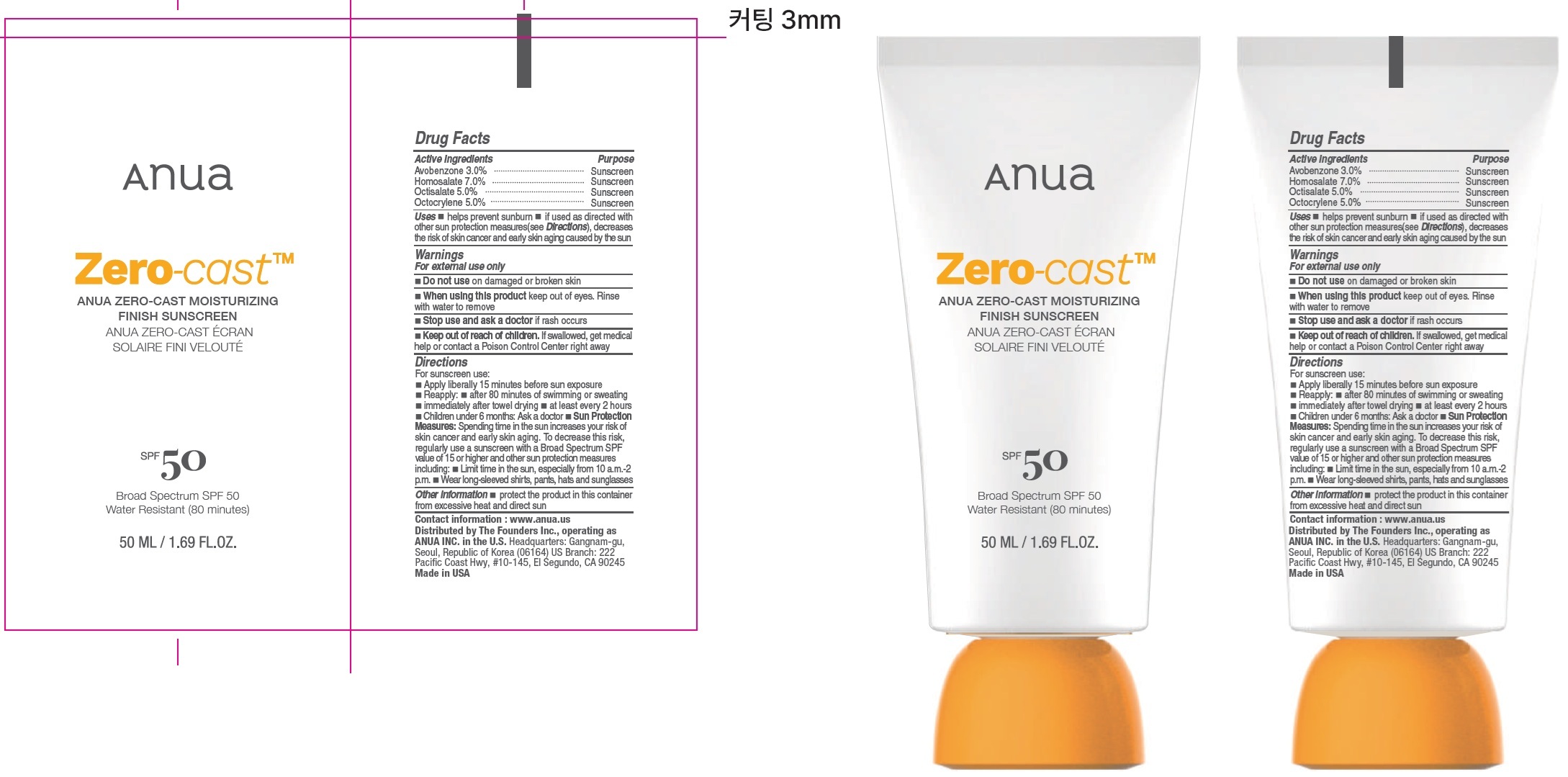 DRUG LABEL: Anua Zero-Cast Moisturizing Finish Sunscreen SPF 50
NDC: 14268-169 | Form: LOTION
Manufacturer: ENGLEWOOD LAB, INC.
Category: otc | Type: HUMAN OTC DRUG LABEL
Date: 20250410

ACTIVE INGREDIENTS: AVOBENZONE 30 mg/1 mL; HOMOSALATE 70 mg/1 mL; OCTISALATE 50 mg/1 mL; OCTOCRYLENE 50 mg/1 mL
INACTIVE INGREDIENTS: WATER; BUTYLOCTYL SALICYLATE; GLYCERIN; DIMETHICONE; CETOSTEARYL ALCOHOL; NIACINAMIDE; SODIUM STEAROYL GLUTAMATE; AMMONIUM POLYACRYLOYLDIMETHYL TAURATE; HYDROXYACETOPHENONE; PHENOXYETHANOL; .ALPHA.-TOCOPHEROL ACETATE; PANTHENOL; PENTAERYTHRITOL TETRAKIS(3-(3,5-DI-TERT-BUTYL-4-HYDROXYPHENYL)PROPIONATE); XANTHAN GUM; 1,2-HEXANEDIOL; SODIUM HYALURONATE

Anua Zero-Cast Moisturizing Finish Sunscreen SPF 50

Active Ingredients

Avobenzone 3.0%
Homosalate 7.0%
Octisalate 5.0%
Octocrylene 5.0%

Purpose

Sunscreen

Uses

- helps prevent sunburn
- if used as directed with other sun protection measures(see Directions), decreases the risk of skin cancer and early skin aging caused by the sun

Warnings

For external use only

Do not use

- on damaged or broken skin

When using this product

- keep out of eyes. Rinse with water to remove

Stop use and ask a doctor

- if rash occurs

Keep out of reach of children.

If swallowed, get medical help or contact a Poison Control Center right away

Directions

- For sunscreen use:
- Apply liberally 15 minutes before sun exposure
- Reapply:
- after 80 minutes of swimming or sweating
- immediately after towel drying
- at least every 2 hours
- Children under 6 months: Ask a doctor
- Sun Protection Measures: Spending time in the sun increases your risk of skin cancer and early skin aging. To decrease this risk, regularly use a sunscreen with a Broad Spectrum SPF value of 15 or higher and other sun protection measures including:
- Limit time in the sun, especially from 10 a.m.-2 p.m.
- Wear long-sleeved shirts, pants, hats and sunglasses

Other information

- protect the product in this container from excessive heat and direct sun

Inactive ingredients

Water (Aqua), Butyloctyl Salicylate, Glycerin, Dimethicone, Poly C10-30 Alkyl Acrylate, VP/Eicosene Copolym er, Cetearyl Alcohol, Niacinamide, So dium Stearoyl Glutamate, Ammonium Polyacryloyldimethyl Taurate, Hydrox yacetophenone, Phenoxyethanol, To copheryl Acetate, Panthenol, Pentaer ythrityl Tetra-Di-T-Butyl Hydroxyhydrocinnamate, Xanthan Gum, 1,2-Hexan ediol, Sodium Hyaluronate

Questions?

+1-888-899-9083 Monday–Friday (9 a.m.–5 p.m. EST) www.anua.us